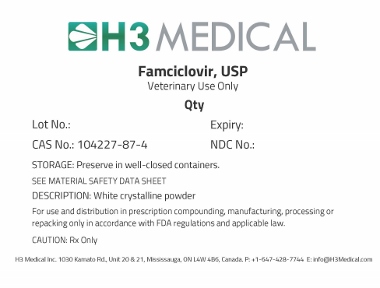 DRUG LABEL: Famciclovir
NDC: 63732-2040 | Form: POWDER
Manufacturer: H3 Medical Inc
Category: other | Type: BULK INGREDIENT - ANIMAL DRUG
Date: 20190905

ACTIVE INGREDIENTS: FAMCICLOVIR 1 g/1 g

Famciclovir